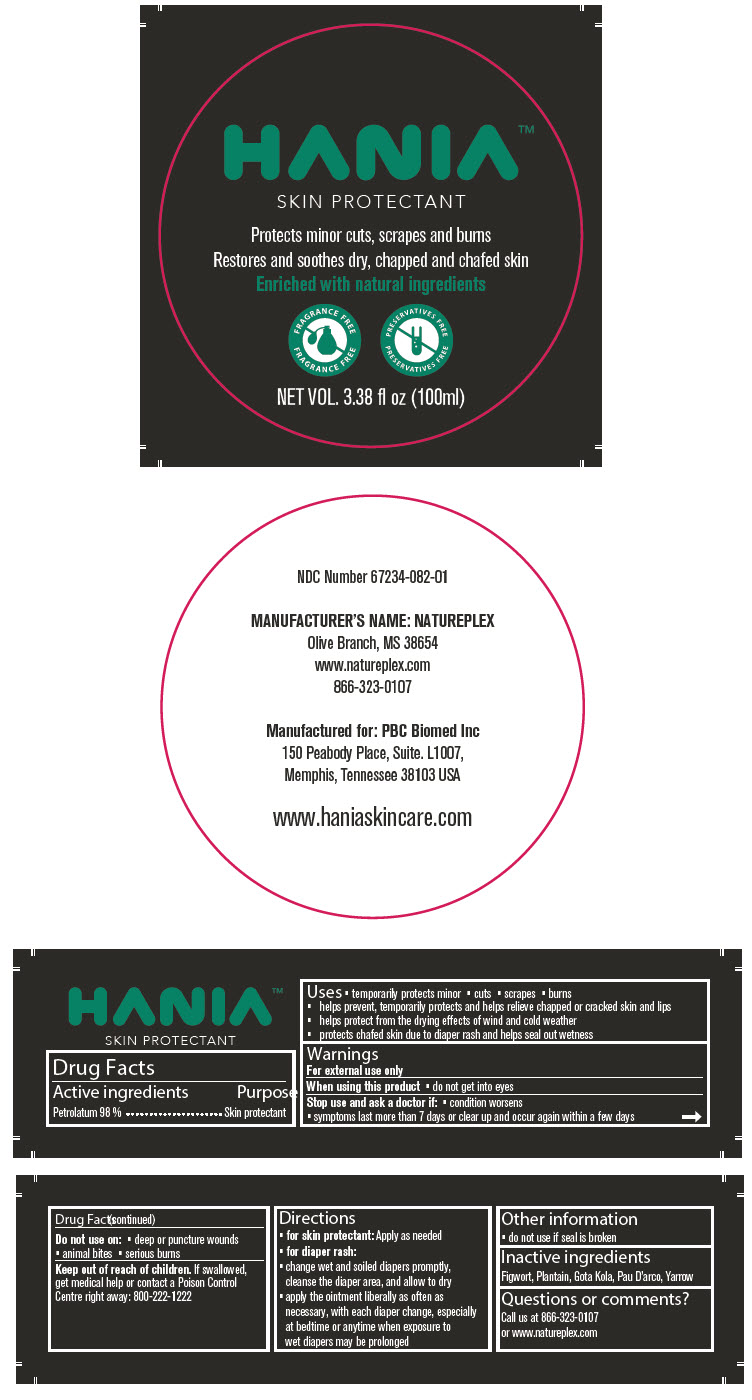 DRUG LABEL: Hania Skin Protectant
NDC: 67234-082 | Form: OINTMENT
Manufacturer: Natureplex LLC
Category: otc | Type: HUMAN OTC DRUG LABEL
Date: 20250219

ACTIVE INGREDIENTS: Petrolatum 98 g/100 mL
INACTIVE INGREDIENTS: SCROPHULARIA NODOSA ROOT; MUSA X PARADISIACA WHOLE; CENTELLA ASIATICA WHOLE; HANDROANTHUS IMPETIGINOSUS WHOLE; ACHILLEA MILLEFOLIUM WHOLE

Hania™ Skin Protectant

Drug Facts

Active ingredients

Petrolatum 98 %

Purpose

Skin protectant

Uses

- temporarily protects minor
- cuts
- scrapes
- burns
- helps prevent, temporarily protects and helps relieve chapped or cracked skin and lips
- helps protect from the drying effects of wind and cold weather
- protects chafed skin due to diaper rash and helps seal out wetness

Warnings

For external use only

When using this product

- do not get into eyes

Stop use and ask a doctor if

- condition worsens
- symptoms last more than 7 days or clear up and occur again within a few days

Do not use on

- deep or puncture wounds
- animal bites
- serious burns

Keep out of reach of children. If swallowed, get medical help or contact a Poison Control Centre right away: 800-222-1222

Directions

- for skin protectant: Apply as needed
- for diaper rash:
  - change wet and soiled diapers promptly, cleanse the diaper area, and allow to dry
  - apply the ointment liberally as often as necessary, with each diaper change, especially at bedtime or anytime when exposure to wet diapers may be prolonged

Other information

- do not use if seal is broken

Inactive ingredients

Figwort, Plantain, Gota Kola, Pau D'arco, Yarrow

Questions or comments?

Call us at 866-323-0107 or www.natureplex.com

PRINCIPAL DISPLAY PANEL - 100 ml Jar Label

HANIA™

SKIN PROTECTANT

Protects minor cuts, scrapes and burns

Restores and soothes dry, chapped and chafed skin

Enriched with natural ingredients

FRAGRANCE FREE
FRAGRANCE FREE

PRESERVATIVES FREE
PRESERVATIVES FREE

NET VOL. 3.38 fl oz (100ml)